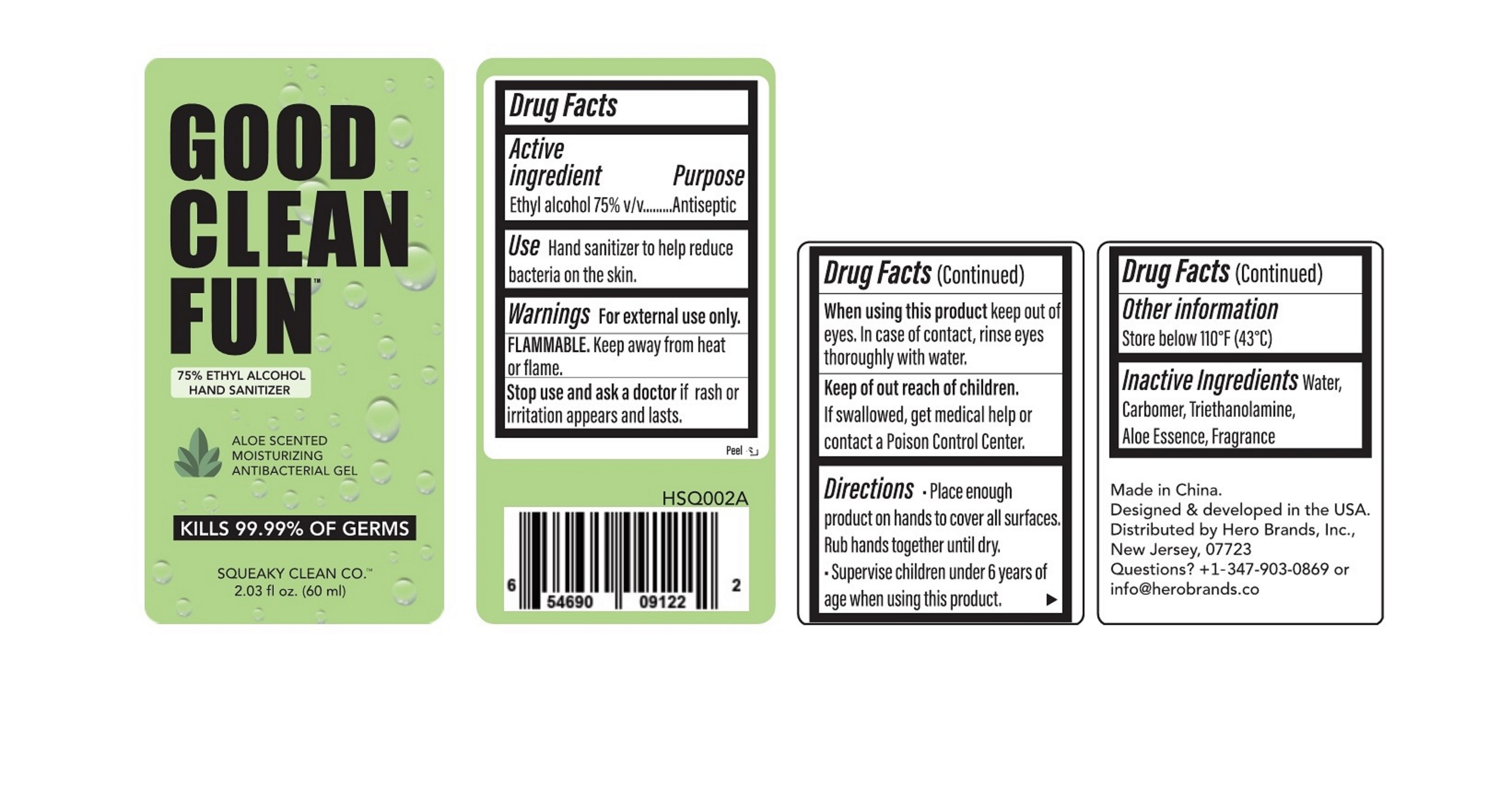 DRUG LABEL: 2oz. Gel Hand Sanitizer Squeeze - Aloe
NDC: 90114-102 | Form: GEL
Manufacturer: Hero Brands, Inc.
Category: otc | Type: HUMAN OTC DRUG LABEL
Date: 20200822

ACTIVE INGREDIENTS: ALCOHOL 75 mL/100 mL
INACTIVE INGREDIENTS: ALOE; ALOE VERA LEAF; CARBOMER HOMOPOLYMER, UNSPECIFIED TYPE; TROLAMINE; WATER

90114-102 60ml 2oz. Gel Hand Sanitizer Squeeze - Aloe

Active Ingredient(s)

Ethyl Alcohol 75% v/v. Purpose: Antiseptic

Purpose

Antiseptic, Hand Sanitizer

Use

Hand Sanitizer to help reduce bacteria on skin.

Warnings

For external use only. Flammable. Keep away from heat or flame

Do not use

- in children less than 2 months of age
- on open skin wounds

When using this product keep out of eyes, In case of contact, rinse eyes thoroughly with water.

Stop use and ask a doctor if rash or irritation appears and lasts.

Keep out of reach of children. If swallowed, get medical help or contact a Poison Control Center.

Directions

- Place enough product on hands to cover all surfaces. Rub hands together until dry.
- Supervise children under 6 years of age when using this product.

Other information

Store below 110°F(43℃).

Inactive ingredients

Water, Carbomer, Triethanolamine, Aloe Essence, Fragrance.

Package Label - Principal Display Panel

60 mL NDC: 90114-102-01